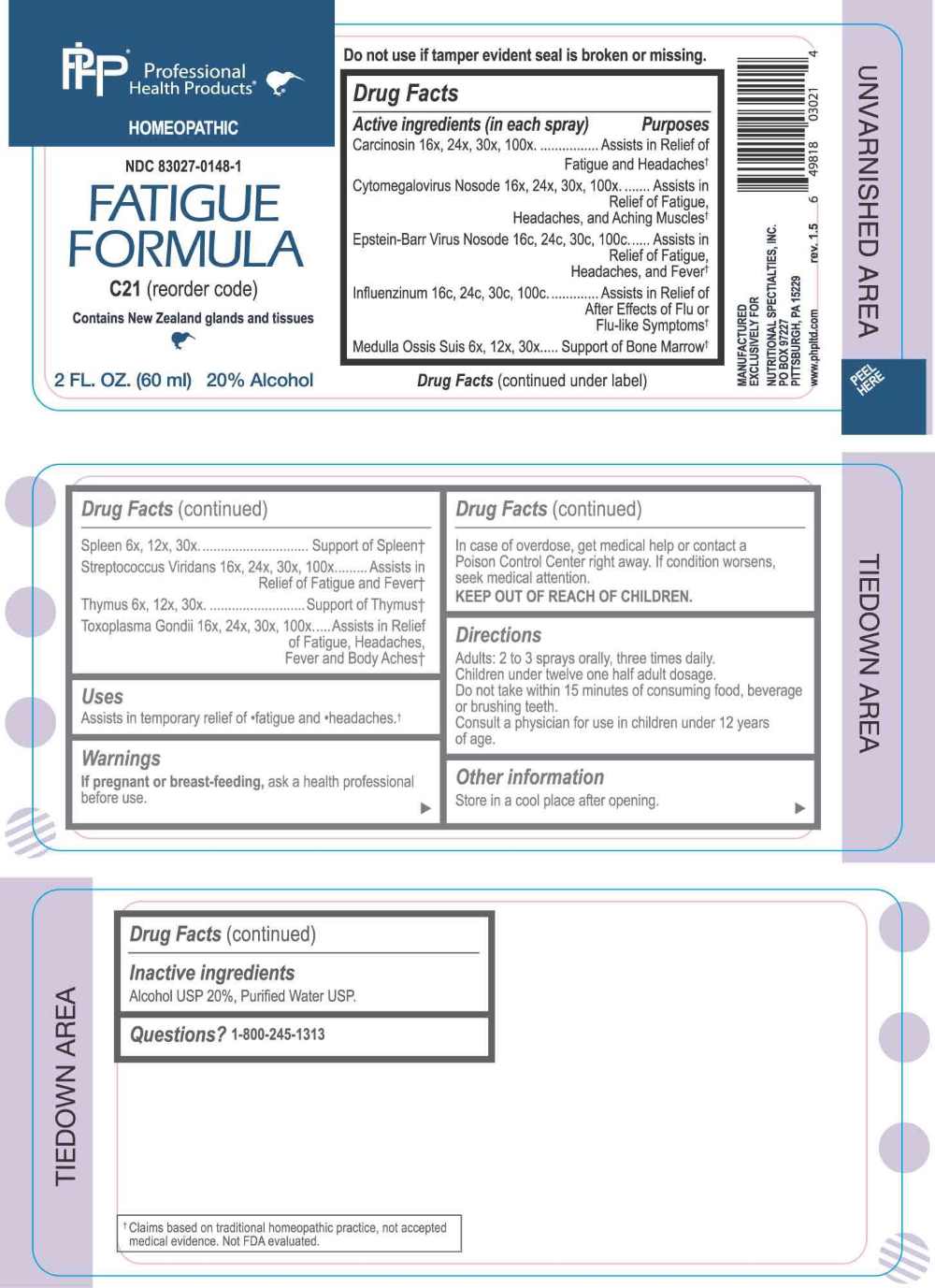 DRUG LABEL: Fatigue Formula
NDC: 83027-0148 | Form: SPRAY
Manufacturer: Nutritional Specialties, Inc.
Category: homeopathic | Type: HUMAN OTC DRUG LABEL
Date: 20250410

ACTIVE INGREDIENTS: SUS SCROFA BONE MARROW 6 [hp_X]/1 mL; BOS TAURUS SPLEEN 6 [hp_X]/1 mL; LAMB 6 [hp_X]/1 mL; HUMAN BREAST TUMOR CELL 16 [hp_X]/1 mL; HUMAN HERPESVIRUS 5 16 [hp_X]/1 mL; INFLUENZA A VIRUS WHOLE 16 [hp_C]/1 mL; INFLUENZA A VIRUS A/DARWIN/6/2021 (H3N2) WHOLE 16 [hp_C]/1 mL; INFLUENZA B VIRUS B/AUSTRIA/1359417/2021 BVR-26 WHOLE 16 [hp_C]/1 mL; INFLUENZA B VIRUS B/PHUKET/3073/2013 BVR-1B WHOLE 16 [hp_C]/1 mL; STREPTOCOCCUS VIRIDANS GROUP 16 [hp_X]/1 mL; TOXOPLASMA GONDII 16 [hp_X]/1 mL; HUMAN HERPESVIRUS 4 16 [hp_C]/1 mL
INACTIVE INGREDIENTS: WATER; ALCOHOL

DRUG FACTS:

ACTIVE INGREDIENTS:

Carcinosin 16X, 24X, 30X, 100X, Cytomegalovirus Nosode 16X, 24X, 30X, 100X, Epstein-Bar Virus Nosode 16C, 24C, 30C, 100C, , Influenzinum 16C, 24C, 30C, 100C, Medulla Ossis Suis 6X, 12X, 30X, Spleen 6X, 12X, 30X, Streptococcus Viridans 16X, 24X, 30X, 100X, Thymus 6X, 12X, 30X, Toxoplasma Gondii 16X, 24X, 30X, 100X.

PURPOSE:

Carcinosin – Assists in Relief of Fatigue and Headaches,† Cytomegalovirus Nosode – Assists in Relief of Fatigue, Headaches, and Aching Muscles,† Epstein-Bar Virus Nosode – Assists in Relief of Fatigue, Headaches, and Fever,† Influenzinum – Assists in Relief of After Effects of Flu or Flu-like Symptoms,† Medulla Ossis Suis – Support of Bone Marrow,† Spleen – Support of Spleen,† Streptococcus Viridans – Assists in Relief of Fatigue and Fever,† Thymus – Support of Thymus,† Toxoplasma Gondii – Assists in Relief of Fatigue, Headaches, Fever and Body Aches†

†Claims based on traditional homeopathic practice, not accepted medical evidence. Not FDA evaluated.

USES:

Assists in temporary relief of fatigue and headaches.†

†Claims based on traditional homeopathic practice, not accepted medical evidence. Not FDA evaluated.

WARNINGS:

If pregnant or breast-feeding, ask a health professional before use.

In case of overdose, get medical help or contact a Poison Control Center right away.

If condition worsens, seek medical attention.

KEEP OUT OF REACH OF CHILDREN

Do not use if tamper evident seal is broken or missing.

Store in a cool place after opening

KEEP OUT OF REACH OF CHILDREN:

In case of overdose, get medical help or contact a Poison Control Center right away.

DIRECTIONS:

Adults: 2 to 3 sprays orally, three times daily. Children under twelve one half adult dosage. Do not take within 15 minutes of consuming food, beverage or brushing teeth. Consult a physician for use in children under 12 years of age.

INACTIVE INGREDIENTS:

Alcohol USP 20%, Purified Water USP.

QUESTIONS:

MANUFACTURED EXCLUSIVELY FOR

NUTRITIONAL SPECIALTIES, INC.

PO BOX 97227

PITTSBURG, PA 15229

www.phpltd.com

1-800-245-1313

PACKAGE LABEL DISPLAY:

Professional

Health Products

HOMEOPATHIC

NDC 83027-0148-1

FATIGUE

FORMULA

2 FL. OZ (60 ml)